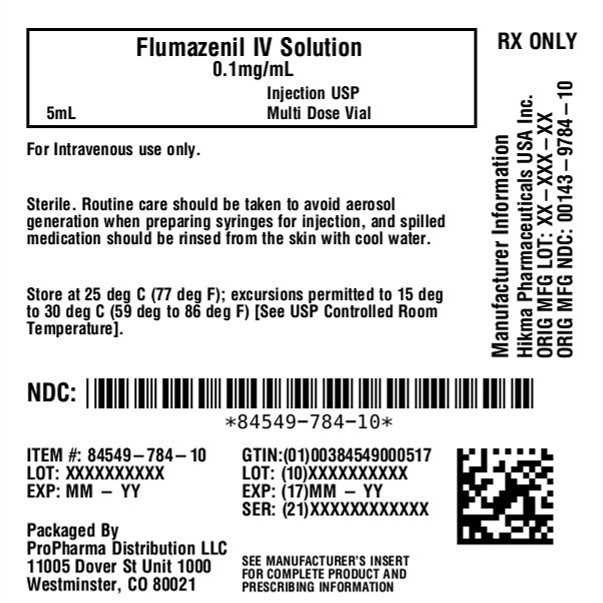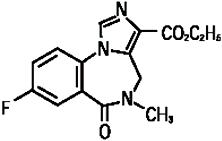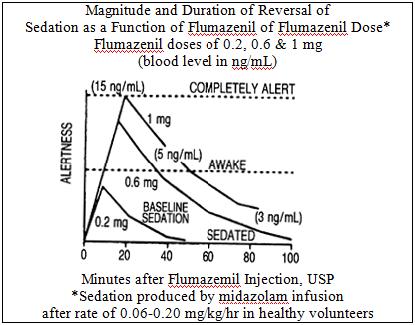 DRUG LABEL: Flumazenil
NDC: 84549-784 | Form: INJECTION, SOLUTION
Manufacturer: ProPharma Distribution
Category: prescription | Type: HUMAN PRESCRIPTION DRUG LABEL
Date: 20251218

ACTIVE INGREDIENTS: FLUMAZENIL 0.1 mg/1 mL
INACTIVE INGREDIENTS: ACETIC ACID 0.1 mg/1 mL; EDETATE DISODIUM 0.1 mg/1 mL; HYDROCHLORIC ACID; METHYLPARABEN 1.8 mg/1 mL; PROPYLPARABEN 0.2 mg/1 mL; SODIUM CHLORIDE 9 mg/1 mL; SODIUM HYDROXIDE

FLUMAZENIL INJECTION, USP

Rx ONLY

DESCRIPTION

Flumazenil Injection, USP is a benzodiazepine receptor antagonist. Chemically, flumazenil is ethyl 8-fluoro-5,6-dihydro-5-methyl-6-oxo-4H-imidazo[1,5-a](1,4) benzodiazepine-3-carboxylate. Flumazenil has an imidazobenzodiazepine structure, a calculated molecular weight of 303.3, and the following structural formula:

Flumazenil is a white to off-white crystalline compound with an octanol: buffer partition coefficient of 14 to 1 at pH 7.4. It is insoluble in water but slightly soluble in acidic aqueous solutions. Flumazenil injection is available as a sterile parenteral dosage form for intravenous administration. Each mL contains 0.1 mg of flumazenil compounded with 1.8 mg of methylparaben, 0.2 mg of propylparaben, 0.9% sodium chloride, 0.01% edetate disodium, and 0.01% acetic acid; the pH is adjusted to approximately 4 with hydrochloric acid and/or, if necessary, sodium hydroxide.

CLINICAL PHARMACOLOGY

Flumazenil, an imidazobenzodiazepine derivative, antagonizes the actions of benzodiazepines on the central nervous system. Flumazenil competitively inhibits the activity at the benzodiazepine recognition site on the GABA/benzodiazepine receptor complex. Flumazenil is a weak partial agonist in some animal models of activity, but has little or no agonist activity in man.

Flumazenil does not antagonize the central nervous system effects of drugs affecting GABA-ergic neurons by means other than the benzodiazepine receptor (including ethanol, barbiturates, or general anesthetics) and does not reverse the effects of opioids.

In animals pretreated with high doses of benzodiazepines over several weeks, flumazenil elicited symptoms of benzodiazepine withdrawal, including seizures. A similar effect was seen in adult human subjects.

Pharmacodynamics

Intravenous flumazenil has been shown to antagonize sedation, impairment of recall, psychomotor impairment and ventilatory depression produced by benzodiazepines in healthy human volunteers.

The duration and degree of reversal of sedative benzodiazepine effects are related to the dose and plasma concentrations of flumazenil as shown in the following data from a study in normal volunteers.

Generally, doses of approximately 0.1 mg to 0.2 mg (corresponding to peak plasma levels of 3 to 6 ng/mL) produce partial antagonism, whereas higher doses of 0.4 to 1 mg (peak plasma levels of 12 to 28 ng/mL) usually produce complete antagonism in patients who have received the usual sedating doses of benzodiazepines. The onset of reversal is usually evident within 1 to 2 minutes after the injection is completed. Eighty percent response will be reached within 3 minutes, with the peak effect occurring at 6 to 10 minutes. The duration and degree of reversal are related to the plasma concentration of the sedating benzodiazepine as well as the dose of flumazenil given.

In healthy volunteers, flumazenil did not alter intraocular pressure when given alone and reversed the decrease in intraocular pressure seen after administration of midazolam.

Pharmacokinetics

After IV administration, plasma concentrations of flumazenil follow a two-exponential decay model. The pharmacokinetics of flumazenil are dose-proportional up to 100 mg.

Distribution

Flumazenil is extensively distributed in the extravascular space with an initial distribution half-life of 4 to 11 minutes and a terminal half-life of 40 to 80 minutes. Peak concentrations of flumazenil are proportional to dose, with an apparent initial volume of distribution of 0.5 L/kg. The volume of distribution at steady-state is 0.9 to 1.1 L/kg. Flumazenil is a weak lipophilic base. Protein binding is approximately 50% and the drug shows no preferential partitioning into red blood cells. Albumin accounts for two thirds of plasma protein binding.

Metabolism

Flumazenil is completely (99%) metabolized. Very little unchanged flumazenil (< 1%) is found in the urine. The major metabolites of flumazenil identified in urine are the de-ethylated free acid and its glucuronide conjugate. In preclinical studies there was no evidence of pharmacologic activity exhibited by the de-ethylated free acid.

Elimination

Elimination of radiolabeled drug is essentially complete within 72 hours, with 90% to 95% of the radioactivity appearing in urine and 5% to 10% in the feces. Clearance of flumazenil occurs primarily by hepatic metabolism and is dependent on hepatic blood flow. In pharmacokinetic studies of normal volunteers, total clearance ranged from 0.8 to 1.0 L/hr/kg.

Pharmacokinetic parameters following a 5-minute infusion of a total of 1 mg of flumazenil mean (coefficient of variation, range):

Cmax(ng/mL) | 24 | (38%, 11 -43)
AUC (ng ·hr/mL) | 15 | (22%, 10-22)
Vss(L/kg) | 1 | (24%, 0.8-1.6)
Cl (L/hr/kg) | 1 | (20%, 0.7-1.4)
Half-life (min) | 54 | (21%, 41-79)

Food Effects

Ingestion of food during an intravenous infusion of the drug results in a 50% increase in clearance, most likely due to the increased hepatic blood flow that accompanies a meal.

Special Populations

The Elderly:

The pharmacokinetics of flumazenil are not significantly altered in the elderly.

Gender:

The pharmacokinetics of flumazenil are not different in male and female subjects.

Renal Failure (creatinine clearance < 10 mL/min) and Hemodialysis:

The pharmacokinetics of flumazenil are not significantly affected.

Patients With Liver Dysfunction:

For patients with moderate liver dysfunction, their mean total clearance is decreased to 40% to 60% and in patients with severe liver dysfunction, it is decreased to 25% of normal value, compared with age-matched healthy subjects. This results in a prolongation of the half-life to 1.3 hours in patients with moderate hepatic impairment and 2.4 hours in severely impaired patients. Caution should be exercised with initial and/or repeated dosing to patients with liver disease.

Drug-Drug Interaction:

The pharmacokinetic profile of flumazenil is unaltered in the presence of benzodiazepine agonists and the kinetic profiles of those benzodiazepines studied (i.e., diazepam, flunitrazepam, lormetazepam, and midazolam) are unaltered by flumazenil. During the 4-hour steady-state and post infusion of ethanol, there were no pharmacokinetic interactions on ethanol mean plasma levels as compared to placebo when flumazenil doses were given intravenously (at 2.5 hours and 6 hours) nor were interactions of ethanol on the flumazenil elimination half-life found.

Pharmacokinetics in Pediatric Patients:

The pharmacokinetics of flumazenil have been evaluated in 29 pediatric patients ranging in age from 1 to 17 years who had undergone minor surgical procedures. The average doses administered were 0.53 mg (0.044 mg/kg) in patients aged 1 to 5years, 0.63 mg (0.020 mg/kg) in patients aged 6 to 12 years, and 0.8 mg (0.014 mg/kg) in patients aged 13 to 17 years. Compared to adults, the elimination half-life in pediatric patients was more variable, averaging 40 minutes (range: 20 to 75 minutes). Clearance and volume of distribution, normalized for body weight, were in the same range as those seen in adults, although more variability was seen in the pediatric patients.

CLINICAL TRIALS

Flumazenil has been administered in adults to reverse the effects of benzodiazepines in conscious sedation, general anesthesia, and the management of suspected benzodiazepine overdose. Limited information from uncontrolled studies in pediatric patients is available regarding the use of flumazenil to reverse the effects of benzodiazepines in conscious sedation only.

Conscious Sedation in Adults

Flumazenil was studied in four trials in 970 patients who received an average of 30 mg diazepam or 10 mg midazolam for sedation (with or without a narcotic) in conjunction with both inpatient and outpatient diagnostic or surgical procedures. Flumazenil was effective in reversing the sedating and psychomotor effects of the benzodiazepine; however, amnesia was less completely and less consistently reversed. In these studies, flumazenil was administered as an initial dose of 0.4 mg IV (two doses of 0.2 mg) with additional 0.2 mg doses as needed to achieve complete awakening, up to a maximum total dose of 1 mg.

Seventy-eight percent of patients receiving flumazenil responded by becoming completely alert. Of those patients, approximately half responded to doses of 0.4 mg to 0.6 mg, while the other half responded to doses of 0.8 mg to 1 mg. Adverse effects were infrequent in patients who received 1 mg of flumazenil or less, although injection site pain, agitation, and anxiety did occur. Reversal of sedation was not associated with any increase in the frequency of inadequate analgesia or increase in narcotic demand in these studies. While most patients remained alert throughout the 3-hour postprocedure observation period, resedation was observed to occur in 3% to 9% of the patients, and was most common in patients who had received high doses of benzodiazepines (see PRECAUTIONS).

General Anesthesia in Adults

Flumazenil was studied in four trials in 644 patients who received midazolam as an induction and/or maintenance agent in both balanced and inhalational anesthesia. Midazolam was generally administered in doses ranging from 5 mg to 80 mg, alone and/or in conjunction with muscle relaxants, nitrous oxide, regional or local anesthetics, narcotics and/or inhalational anesthetics. Flumazenil was given as an initial dose of 0.2 mg IV, with additional 0.2 mg doses as needed to reach a complete response, up to a maximum total dose of 1 mg. These doses were effective in reversing sedation and restoring psychomotor function, but did not completely restore memory as tested by picture recall. Flumazenil was not as effective in the reversal of sedation in patients who had received multiple anesthetic agents in addition to benzodiazepines.

Eighty-one percent of patients sedated with midazolam responded to flumazenil by becoming completely alert or just slightly drowsy. Of those patients, 36% responded to doses of 0.4 mg to 0.6 mg, while 64% responded to doses of 0.8 mg to 1 mg.

Resedation in patients who responded to flumazenil occurred in 10% to 15% of patients studied and was more common with larger doses of midazolam (> 20 mg), long procedures (>60 minutes) and use of neuromuscular blocking agents (see PRECAUTIONS).

Management of Suspected Benzodiazepine Overdose in Adults

Flumazenil was studied in two trials in 497 patients who were presumed to have taken an overdose of a benzodiazepine, either alone or in combination with a variety of other agents. In these trials, 299 patients were proven to have taken a benzodiazepine as part of the overdose, and 80% of the 148 who received flumazenil responded by an improvement in level of consciousness. Of the patients who responded to flumazenil, 75% responded to a total dose of 1 mg to 3 mg.

Reversal of sedation was associated with an increased frequency of symptoms of CNS excitation. Of the patients treated with flumazenil, 1% to 3% were treated for agitation or anxiety. Serious side effects were uncommon, but six seizures were observed in 446 patients treated with flumazenil in these studies. Four of these 6 patients had ingested a large dose of cyclic antidepressants, which increased the risk of seizures (see WARNINGS).

INDIVIDUALIZATION OF DOSAGE

General Principles

The serious adverse effects of flumazenil are related to the reversal of benzodiazepine effects. Using more than the minimally effective dose of flumazenil is tolerated by most patients but may complicate the management of patients who are physically dependent on benzodiazepines or patients who are depending on benzodiazepines for therapeutic effect (such as suppression of seizures in cyclic antidepressant overdose).

In high-risk patients, it is important to administer the smallest amount of flumazenil that is effective. The 1-minute wait between individual doses in the dose-titration recommended for general clinical populations may be too short for high-risk patients. This is because it takes 6 to 10 minutes for any single dose of flumazenil to reach full effects. Practitioners should slow the rate of administration of flumazenil administered to high-risk patients as recommended below.

Anesthesia and Conscious Sedation in Adult Patients

Flumazenil is well tolerated at the recommended doses in individuals who have no tolerance to (or dependence on) benzodiazepines. The recommended doses and titration rates in anesthesia and conscious sedation (0.2 mg to 1 mg given at 0.2 mg/min) are well tolerated in patients receiving the drug for reversal of a single benzodiazepine exposure in most clinical settings (see ADVERSE REACTIONS). The major risk will be resedation because the duration of effect of a long-acting (or large dose of a short-acting) benzodiazepine may exceed that of flumazenil injection. Resedation may be treated by giving a repeat dose at no less than 20-minute intervals. For repeat treatment, no more than 1 mg (at 0.2 mg/min doses) should be given at any one time and no more than 3 mg should be given in any one hour.

Benzodiazepine Overdose in Adult Patients

The risk of confusion, agitation, emotional lability, and perceptual distortion with the doses recommended in patients with benzodiazepine overdose (3 mg to 5 mg administered as 0.5 mg/min) may be greater than that expected with lower doses and slower administration. The recommended doses represent a compromise between a desirable slow awakening and the need for prompt response and a persistent effect in the overdose situation. If circumstances permit, the physician may elect to use the 0.2 mg/minute titration rate to slowly awaken the patient over 5 to 10 minutes, which may help to reduce signs and symptoms on emergence.

Flumazenil has no effect in cases where benzodiazepines are not responsible for sedation. Once doses of 3 mg to 5 mg have been reached without clinical response, additional flumazenil is likely to have no effect.

Patients Tolerant to Benzodiazepines

Flumazenil may cause benzodiazepine withdrawal symptoms in individuals who have been taking benzodiazepines long enough to have some degree of tolerance. Patients who had been taking benzodiazepines prior to entry into the flumazenil trials, who were given flumazenil in doses over 1 mg, experienced withdrawal-like events 2 to 5 times more frequently than patients who received less than 1 mg.

In patients who may have tolerance to benzodiazepines, as indicated by clinical history or by the need for larger than usual doses of benzodiazepines, slower titration rates of 0.1 mg/min and lower total doses may help reduce the frequency of emergent confusion and agitation. In such cases, special care must be taken to monitor the patients for resedation because of the lower doses of flumazenil used.

Patients Physically Dependent on Benzodiazepines

Flumazenil is known to precipitate withdrawal seizures in patients who are physically dependent on benzodiazepines, even if such dependence was established in a relatively few days of high-dose sedation in Intensive Care Unit (ICU) environments. The risk of either seizures or resedation in such cases is high and patients have experienced seizures before regaining consciousness. Flumazenil should be used in such settings with extreme caution, since the use of flumazenil in this situation has not been studied and no information as to dose and rate of titration is available. Flumazenil should be used in such patients only if the potential benefits of using the drug outweigh the risks of precipitated seizures. Physicians are directed to the scientific literature for the most current information in this area.

INDICATIONS AND USAGE

Adult Patients

Flumazenil Injection, USP is indicated for the complete or partial reversal of the sedative effects of benzodiazepines in cases where general anesthesia has been induced and/or maintained with benzodiazepines, where sedation has been produced with benzodiazepines for diagnostic and therapeutic procedures, and for the management of benzodiazepine overdose.

Pediatric Patients (aged 1 to 17)

Flumazenil Injection, USP is indicated for the reversal of conscious sedation induced with benzodiazepines (see PRECAUTIONS: Pediatric Use).

CONTRAINDICATIONS

Flumazenil is contraindicated:

- in patients with a known hypersensitivity to flumazenil or benzodiazepines.
- in patients who have been given a benzodiazepine for control of a potentially life-threatening condition (e.g., control of intracranial pressure or status epilepticus).
- in patients who are showing signs of serious cyclic antidepressant overdose (see WARNINGS).

WARNINGS

BOXED WARNING

THE USE OFFLUMAZENILHAS BEEN ASSOCIATED WITH THE OCCURRENCE OF SEIZURES.

THESE ARE MOST FREQUENT IN PATIENTS WHO HAVE BEEN ON BENZODIAZEPINES FOR LONG-TERM SEDATION OR IN OVERDOSE CASES WHERE PATIENTS ARE SHOWING SIGNS OF SERIOUS CYCLIC ANTIDEPRESSANT OVERDOSE.

PRACTITIONERS SHOULD INDIVIDUALIZE THE DOSAGE OFFLUMAZENILAND BE PREPARED TO MANAGE SEIZURES.

Risk of Seizures

The reversal of benzodiazepine effects may be associated with the onset of seizures in certain high-risk populations. Possible risk factors for seizures include: concurrent major sedative-hypnotic drug withdrawal, recent therapy with repeated doses of parenteral benzodiazepines, myoclonic jerking or seizure activity prior to flumazenil administration in overdose cases, or concurrent cyclic antidepressant poisoning.

Flumazenil is not recommended in cases of serious cyclic antidepressant poisoning, as manifested by motor abnormalities (twitching, rigidity, focal seizure), dysrhythmia (wide QRS, ventricular dysrhythmia, heart block), anticholinergic signs (mydriasis, dry mucosa, hypoperistalsis), and cardiovascular collapse at presentation. In such cases flumazenil should be withheld and the patient should be allowed to remain sedated (with ventilatory and circulatory support as needed) until the signs of antidepressant toxicity have subsided. Treatment with flumazenil has no known benefit to the seriously ill mixed-overdose patient other than reversing sedation and should not be used in cases where seizures (from any cause) are likely.

Most convulsions associated with flumazenil administration require treatment and have been successfully managed with benzodiazepines, phenytoin or barbiturates. Because of the presence of flumazenil, higher than usual doses of benzodiazepines may be required.

Hypoventilation

Patients who have received flumazenil for the reversal of benzodiazepine effects (after conscious sedation or general anesthesia) should be monitored for resedation, respiratory depression, or other residual benzodiazepine effects for an appropriate period (up to 120 minutes) based on the dose and duration of effect of the benzodiazepine employed.

This is because flumazenil has not been established in patients as an effective treatment for hypoventilation due to benzodiazepine administration. In healthy male volunteers, flumazenil is capable of reversing benzodiazepine-induced depression of the ventilatory responses to hypercapnia and hypoxia after a benzodiazepine alone. However, such depression may recur because the ventilatory effects of typical doses of flumazenil (1 mg or less) may wear off before the effects of many benzodiazepines. The effects of flumazenil on ventilatory response following sedation with a benzodiazepine in combination with an opioid are inconsistent and have not been adequately studied. The availability of flumazenil does not diminish the need for prompt detection of hypoventilation and the ability to effectively intervene by establishing an airway and assisting ventilation.

Overdose cases should always be monitored for resedation until the patients are stable and resedation is unlikely.

PRECAUTIONS

Return of Sedation

Flumazenil may be expected to improve the alertness of patients recovering from a procedure involving sedation or anesthesia with benzodiazepines, but should not be substituted for an adequate period of postprocedure monitoring. The availability of flumazenil does not reduce the risks associated with the use of large doses of benzodiazepines for sedation.

Patients should be monitored for resedation, respiratory depression (see WARNINGS) or other persistent or recurrent agonist effects for an adequate period of time after administration of flumazenil.

Resedation is least likely in cases where flumazenil is administered to reverse a low dose of a short-acting benzodiazepine (<10 mg midazolam). It is most likely in cases where a large single or cumulative dose of a benzodiazepine has been given in the course of a long procedure along with neuromuscular blocking agents and multiple anesthetic agents.

Profound resedation was observed in 1% to 3% of adult patients in the clinical studies. In clinical situations where resedation must be prevented in adult patients, physicians may wish to repeat the initial dose (up to 1 mg of flumazenil given at 0.2 mg/min) at 30 minutes and possibly again at 60 minutes. This dosage schedule, although not studied in clinical trials, was effective in preventing resedation in a pharmacologic study in normal volunteers.

The use of flumazenil to reverse the effects of benzodiazepines used for conscious sedation has been evaluated in one open-label clinical trial involving 107 pediatric patients between the ages of 1 and 17 years. This study suggested that pediatric patients who have become fully awake following treatment with flumazenil may experience a recurrence of sedation, especially younger patients (ages 1 to 5) .Resedation was experienced in 7 of 60 patients who were fully alert 10 minutes after the start of flumazenil administration. No patient experienced a return to the baseline level of sedation. Mean time to resedation was 25 minutes (range: 19 to 50 minutes) (see PRECAUTIONS: Pediatric Use). The safety and effectiveness of repeated flumazenil administration in pediatric patients experiencing resedation have not been established.

Use in the ICU

Flumazenil should be used with caution in the ICU because of the increased risk of unrecognized benzodiazepine dependence in such settings. Flumazenil may produce convulsions in patients physically dependent on benzodiazepines (see INDIVIDUALIZATION OF DOSAGE and WARNINGS).

Administration of flumazenil to diagnose benzodiazepine-induced sedation in the ICU is not recommended due to the risk of adverse events as described above. In addition, the prognostic significance of a patient’s failure to respond to flumazenil in cases confounded by metabolic disorder, traumatic injury, drugs other than benzodiazepines, or any other reasons not associated with benzodiazepine receptor occupancy is unknown.

Use in Benzodiazepine Overdosage

Flumazenil is intended as an adjunct to, not as a substitute for, proper management of airway, assisted breathing, circulatory access and support, internal decontamination by lavage and charcoal, and adequate clinical evaluation.

Necessary measures should be instituted to secure airway, ventilation and intravenous access prior to administering flumazenil. Upon arousal, patients may attempt to withdraw endotracheal tubes and/or intravenous lines as the result of confusion and agitation following awakening.

Head Injury

Flumazenil should be used with caution in patients with head injury as it may be capable of precipitating convulsions or altering cerebral blood flow in patients receiving benzodiazepines. It should be used only by practitioners prepared to manage such complications should they occur.

Use With Neuromuscular Blocking Agents

Flumazenil should not be used until the effects of neuromuscular blockade have been fully reversed.

Use in Psychiatric Patients

Flumazenil has been reported to provoke panic attacks in patients with a history of panic disorder.

Pain on Injection

To minimize the likelihood of pain or inflammation at the injection site, flumazenil should be administered through a freely flowing intravenous infusion into a large vein. Local irritation may occur following extravasation into perivascular tissues.

Use in Respiratory Disease

The primary treatment of patients with serious lung disease who experience serious respiratory depression due to benzodiazepines should be appropriate ventilatory support (see PRECAUTIONS) rather than the administration of flumazenil injection. Flumazenil is capable of partially reversing benzodiazepine-induced alterations in ventilatory drive in healthy volunteers, but has not been shown to be clinically effective.

Use in Cardiovascular Disease

Flumazenil did not increase the work of the heart when used to reverse benzodiazepines in cardiac patients when given at a rate of 0. 1 mg/min in total doses of less than 0.5 mg in studies reported in the clinical literature. Flumazenil alone had no significant effects on cardiovascular parameters when administered to patients with stable ischemic heart disease.

Use in Liver Disease

The clearance of flumazenil is reduced to 40% to 60% of normal in patients with mild to moderate hepatic disease and to 25% of normal in patients with severe hepatic dysfunction (see CLINICAL PHARMACOLOGY: Pharmacokinetics). While the dose of flumazenil used for initial reversal of benzodiazepine effects is not affected, repeat doses of the drug in liver disease should be reduced in size or frequency.

Use in Drug- and Alcohol-Dependent Patients

Flumazenil should be used with caution in patients with alcoholism and other drug dependencies due to the increased frequency of benzodiazepine tolerance and dependence observed in these patient populations.

Flumazenil is not recommended either as a treatment for benzodiazepine dependence or for the management of protracted benzodiazepine abstinence syndromes, as such use has not been studied.

The administration of flumazenil can precipitate benzodiazepine withdrawal in animals and man. This has been seen in healthy volunteers treated with therapeutic doses of oral lorazepam for up to 2 weeks who exhibited effects such as hot flushes, agitation and tremor when treated with cumulative doses of up to 3 mg doses of flumazenil.

Similar adverse experiences suggestive of flumazenil precipitation of benzodiazepine withdrawal have occurred in some adult patients in clinical trials. Such patients had a short-lived syndrome characterized by dizziness, mild confusion, emotional lability, agitation (with signs and symptoms of anxiety), and mild sensory distortions. This response was dose-related, most common at doses above 1 mg, rarely required treatment other than reassurance and was usually short lived. When required, these patients (5 to 10 cases) were successfully treated with usual doses of a barbiturate, a benzodiazepine, or other sedative drug.

Practitioners should assume that flumazenil administration may trigger dose-dependent withdrawal syndromes in patients with established physical dependence on benzodiazepines and may complicate the management of withdrawal syndromes for alcohol, barbiturates and cross-tolerant sedatives.

Drug Interactions

Interaction with central nervous system depressants other than benzodiazepines has not been specifically studied; however, no deleterious interactions were seen when flumazenil was administered after narcotics, inhalational anesthetics, muscle relaxants and muscle relaxant antagonists administered in conjunction with sedation or anesthesia.

Particular caution is necessary when using flumazenil in cases of mixed drug overdosage since the toxic effects (such as convulsions and cardiac dysrhythmias) of other drugs taken in overdose (especially cyclic antidepressants) may emerge with the reversal of the benzodiazepine effect by flumazenil (see WARNINGS).

The use of flumazenil is not recommended in epileptic patients who have been receiving benzodiazepine treatment for a prolonged period. Although flumazenil exerts a slight intrinsic anticonvulsant effect, its abrupt suppression of the protective effect of a benzodiazepine agonist can give rise to convulsions in epileptic patients.

Flumazenil blocks the central effects of benzodiazepines by competitive interaction at the receptor level. The effects of nonbenzodiazepine agonists at benzodiazepine receptors, such as zopiclone, triazolopyridazines and others, are also blocked by flumazenil.

The pharmacokinetics of benzodiazepines are unaltered in the presence of flumazenil and vice versa.

There is no pharmacokinetic interaction between ethanol and flumazenil.

Use in Ambulatory Patients

The effects of flumazenil may wear off before a long-acting benzodiazepine is completely cleared from the body. In general, if a patient shows no signs of sedation within 2 hours after a 1-mg dose of flumazenil, serious resedation at a later time is unlikely. An adequate period of observation must be provided for any patient in whom either long-acting benzodiazepines (such as diazepam) or large doses of short-acting benzodiazepines (such as >10 mg of midazolam) have been used (see INDIVIDUALIZATION OF DOSAGE).

Because of the increased risk of adverse reactions in patients who have been taking benzodiazepines on a regular basis, it is particularly important that physicians query patients or their guardians carefully about benzodiazepine, alcohol and sedative use as part of the history prior to any procedure in which the use of flumazenil is planned (see PRECAUTIONS: Use in Drug- and Alcohol-Dependent Patients).

Information for Patients

Flumazenil does not consistently reverse amnesia. Patients cannot be expected to remember information told to them in the postprocedure period and instructions given to patients should be reinforced in writing or given to a responsible family member. Physicians are advised to discuss with patients or their guardians, both before surgery and at discharge, that although the patient may feel alert at the time of discharge, the effects of the benzodiazepine (e.g., sedation) may recur. As a result, the patient should be instructed, preferably in writing, that their memory and judgment may be impaired and specifically advised:

1. Not to engage in any activities requiring complete alertness, and not to operate hazardous machinery or a motor vehicle during the first 24 hours after discharge, and it is certain no residual sedative effects of the benzodiazepine remain.
2. Not to take any alcohol or non-prescription drugs during the first 24 hours after flumazenil administration or if the effects of the benzodiazepine persist.

Laboratory Tests

No specific laboratory tests are recommended to follow the patient’s response or to identify possible adverse reactions.

Drug/Laboratory Test Interactions

The possible interaction of flumazenil with commonly used laboratory tests has not been evaluated.

Carcinogenesis, Mutagenesis, Impairment of Fertility

Carcinogenesis:

No studies in animals to evaluate the carcinogenic potential of flumazenil have been conducted.

Mutagenesis:

No evidence for mutagenicity was noted in the Ames test using five different tester strains. Assays for mutagenic potential in S. cerevisiaeD7 and in Chinese hamster cells were considered to be negative as were blastogenesis assays in vitroin peripheral human lymphocytes and in vivoin a mouse micronucleus assay. Flumazenil caused a slight increase in unscheduled DNA synthesis in rat hepatocyte culture at concentrations which were also cytotoxic; no increase in DNA repair was observed in male mouse germ cells in an in vivoDNA repair assay.

Impairment of Fertility:

A reproduction study in male and female rats did not show any impairment of fertility at oral dosages of 125 mg/kg/day. From the available data on the area under the curve (AUC) in animals and man the dose represented 120x the human exposure from a maximum recommended intravenous dose of 5 mg.

Pregnancy

Pregnancy Category C:

There are no adequate and well-controlled studies of the use of flumazenil in pregnant women. Flumazenil should be used during pregnancy only if the potential benefit justifies the potential risk to the fetus.

Teratogenic Effects:

Flumazenil has been studied for teratogenicity in rats and rabbits following oral treatments of up to 150 mg/kg/day. The treatments during the major organogenesis were on days 6 to 15 of gestation in the rat and days 6 to 18 of gestation in the rabbit. No teratogenic effects were observed in rats or rabbits at 150 mg/kg; the dose, based on the available data on the area under the plasma concentration-time curve (AUC) represented 120x to 600x the human exposure from a maximum recommended intravenous dose of 5 mg in humans. In rabbits, embryocidal effects (as evidenced by increased preimplantation and postimplantation losses) were observed at 50 mg/kg or 200x the human exposure from a maximum recommended intravenous dose of 5 mg. The no-effect dose of 15 mg/kg in rabbits represents 60x the human exposure.

Nonteratogenic Effects:

An animal reproduction study was conducted in rats at oral dosages of 5, 25, and 125 mg/kg/day of flumazenil. Pup survival was decreased during the lactating period, pup liver weight at weaning was increased for the high-dose group (125 mg/kg/day) and incisor eruption and ear opening in the offspring were delayed; the delay in ear opening was associated with a delay in the appearance of the auditory startle response. No treatment-related adverse effects were noted for the other dose groups. Based on the available data from AUC, the effect level (125 mg/kg) represents 120x the human exposure from 5 mg, the maximum recommended intravenous dose in humans. The no-effect level represents 24x the human exposure from an intravenous dose of 5 mg.

Labor and Delivery

The use of flumazenil to reverse the effects of benzodiazepines used during labor and delivery is not recommended because the effects of the drug in the newborn are unknown.

Nursing Mothers

Caution should be exercised when deciding to administer flumazenil to a nursing woman because it is not known whether flumazenil is excreted in human milk.

Pediatric Use

The safety and effectiveness of flumazenil have been established in pediatric patients 1 year of age and older. Use of flumazenil in this age group is supported by evidence from adequate and well-controlled studies of flumazenil in adults with additional data from uncontrolled pediatric studies including one open-label trial.

The use of flumazenil to reverse the effects of benzodiazepines used for conscious sedation was evaluated in one uncontrolled clinical trial involving 107 pediatric patients between the ages of 1 and 17 years. At the doses used, flumazenil’s safety was established in this population. Patients received up to 5 injections of 0.01 mg/kg flumazenil up to a maximum total dose of 1.0 mg at a rate not exceeding 0.2 mg/min.

Of 60 patients who were fully alert at 10 minutes, 7 experienced resedation. Resedation occurred between 19 and 50 minutes after the start of flumazenil administration. None of the patients experienced a return to the baseline level of sedation. All 7 patients were between the ages of 1 and 5 years. The types and frequency of adverse events noted in these pediatric patients were similar to those previously documented in clinical trials with flumazenil to reverse conscious sedation in adults. No patient experienced a serious adverse event attributable to flumazenil.

The safety and efficacy of flumazenil in the reversal of conscious sedation in pediatric patients below the age of 1 year have not been established (see CLINICAL PHARMACOLOGY: Pharmacokinetics in Pediatric Patients).

The safety and efficacy of flumazenil have not been established in pediatric patients for reversal of the sedative effects of benzodiazepines used for induction of general anesthesia, for the management of overdose, or for the resuscitation of the newborn, as no well-controlled clinical studies have been performed to determine the risks, benefits and dosages to be used. However, published anecdotal reports discussing the use of flumazenil in pediatric patients for these indications have reported similar safety profiles and dosing guidelines to those described for the reversal of conscious sedation.

The risks identified in the adult population with flumazenil use also apply to pediatric patients. Therefore, consult the CONTRAINDICATIONS, WARNINGS, PRECAUTIONS, and ADVERSE REACTIONSsections when using flumazenil in pediatric patients.

Geriatric Use

Of the total number of subjects in clinical studies of flumazenil, 248 were 65 and over. No overall differences in safety or effectiveness were observed between these subjects and younger subjects. Other reported clinical experience has not identified differences in responses between the elderly and younger patients, but greater sensitivity of some older individuals cannot be ruled out.

The pharmacokinetics of flumazenil have been studied in the elderly and are not significantly different from younger patients. Several studies of flumazenil in subjects over the age of 65 and one study in subjects over the age of 80 suggest that while the doses of benzodiazepine used to induce sedation should be reduced, ordinary doses of flumazenil may be used for reversal.

ADVERSE REACTIONS

Serious Adverse Reactions

Deaths have occurred in patients who received flumazenil in a variety of clinical settings. The majority of deaths occurred in patients with serious underlying disease or in patients who had ingested large amounts of non-benzodiazepine drugs (usually cyclic antidepressants), as part of an overdose.

Serious adverse events have occurred in all clinical settings, and convulsions are the most common serious adverse events reported. Flumazenil administration has been associated with the onset of convulsions in patients with severe hepatic impairment and in patients who are relying on benzodiazepine effects to control seizures, are physically dependent on benzodiazepines, or who have ingested large doses of other drugs (mixed-drug overdose) (see WARNINGS).

Two of the 446 patients who received flumazenil in controlled clinical trials for the management of a benzodiazepine overdose had cardiac dysrhythmias (1 ventricular tachycardia,1 junctional tachycardia).

Adverse Events in Clinical Studies

The following adverse reactions were considered to be related to flumazenil administration (both alone and for the reversal of benzodiazepine effects) and were reported in studies involving 1875 individuals who received flumazenil in controlled trials. Adverse events most frequently associated with flumazenil alone were limited to dizziness, injection site pain, increased sweating, headache, and abnormal or blurred vision (3% to 9%).

Body as a Whole:fatigue (asthenia, malaise), headache, injection site pain*, injection site reaction (thrombophlebitis, skin abnormality, rash)

Cardiovascular System:cutaneous vasodilation (sweating, flushing, hot flushes)

Digestive System:nausea, vomiting (11%)

Nervous System:agitation (anxiety, nervousness, dry mouth, tremor, palpitations, insomnia, dyspnea, hyperventilation)*, dizziness (vertigo, ataxia) (10%), emotional lability (crying abnormal, depersonalization, euphoria, increased tears, depression, dysphoria, paranoia)

Special Senses:abnormal vision (visual field defect, diplopia), paresthesia (sensation abnormal, hypoesthesia)

All adverse reactions occurred in 1% to 3% of cases unless otherwise marked.

* indicates reaction in 3% to 9% of cases.

Observed percentage reported if greater than 9%.

The following adverse events were observed infrequently (less than 1%) in the clinical studies, but were judged as probably related to flumazenil administration and/or reversal of benzodiazepine effects:

Nervous System:confusion (difficulty concentrating, delirium), convulsions (see WARNINGS), somnolence (stupor)

Special Senses:abnormal hearing (transient hearing impairment, hyperacusis, tinnitus)

The following adverse events occurred with frequencies less than 1% in the clinical trials. Their relationship to flumazenil administration is unknown, but they are included as alerting information for the physician.

Body as a Whole:rigors, shivering

Cardiovascular System:arrhythmia (atrial, nodal, ventricular extrasystoles), bradycardia, tachycardia, hypertension, chest pain

Digestive System:hiccup

Nervous System:speech disorder (dysphonia, thick tongue)

Not included in this list is operative site pain that occurred with the same frequency in patients receiving placebo as in patients receiving flumazenil for reversal of sedation following a surgical procedure.

Additional Adverse Reactions Reported During Post-marketing Experience

The following events have been reported during postapproval use of flumazenil.

Nervous System:Fear, panic attacks in patients with a history of panic disorders.

Withdrawal symptoms may occur following rapid injection of flumazenil in patients with long-term exposure to benzodiazepines.

To report SUSPECTED ADVERSE REACTIONS, contact Hikma Pharmaceutical USA Inc. at 1-877-845-0689 or the FDA at 1-800-FDA-1088 or www.fda.gov/medwatch.

DRUG ABUSE AND DEPENDENCE

Flumazenil acts as a benzodiazepine antagonist, blocks the effect of benzodiazepines in animals and man, antagonizes benzodiazepine reinforcement in animal models, produces dysphoria in normal subjects, and has had no reported abuse in foreign marketing.

Although flumazenil has a benzodiazepine-like structure it does not act as a benzodiazepine agonist in man and is not a controlled substance.

OVERDOSAGE

There is limited experience of acute overdosage with flumazenil.

There is no specific antidote for overdose with flumazenil. Treatment of an overdose with flumazenil injection should consist of general supportive measures including monitoring of vital signs and observation of the clinical status of the patient.

Intravenous bolus administration of doses ranging from 2.5 to 100 mg (exceeding those recommended) of flumazenil, when administered to healthy normal volunteers in the absence of a benzodiazepine agonist, produced no serious adverse reactions, severe signs or symptoms, or clinically significant laboratory test abnormalities. In clinical studies, most adverse reactions to flumazenil were an extension of the pharmacologic effects of the drug in reversing benzodiazepine effects.

Reversal with an excessively high dose of flumazenil injection may produce anxiety, agitation, increased muscle tone, hyperesthesia and possibly convulsions. Convulsions have been treated with barbiturates, benzodiazepines and phenytoin, generally with prompt resolution of the seizures (see WARNINGS).

DOSAGE AND ADMINISTRATION

Flumazenil injection is recommended for intravenous use only. It is compatible with 5% dextrose in water, lactated Ringer’s and normal saline solutions. If flumazenil injection is drawn into a syringe or mixed with any of these solutions, it should be discarded after 24 hours. For optimum sterility, flumazenil injection should remain in the vial until just before use. As with all parenteral drug products, flumazenil injection should be inspected visually for particulate matter and discoloration prior to administration, whenever solution and container permit.

To minimize the likelihood of pain at the injection site, flumazenil injection should be administered through a freely running intravenous infusion into a large vein.

Reversal of Conscious Sedation

Adult Patients

For the reversal of the sedative effects of benzodiazepines administered for conscious sedation, the recommended initial dose of flumazenil injection is 0.2 mg (2 mL) administered intravenously over 15 seconds. If the desired level of consciousness is not obtained after waiting an additional 45 seconds, a second dose of 0.2 mg (2 mL) can be injected and repeated at 60-second intervals where necessary (up to a maximum of 4 additional times) to a maximum total dose of 1 mg (10 mL). The dosage should be individualized based on the patient’s response, with most patients responding to doses of 0.6 mg to 1 mg (see INDIVIDUALIZATION OF DOSAGE).

In the event of resedation, repeated doses may be administered at 20-minute intervals as needed. For repeat treatment, no more than 1 mg (given as 0.2 mg/min) should be administered at any one time, and no more than 3 mg should be given in any one hour.

It is recommended that flumazenil injection be administered as the series of small injections described (not as a single bolus injection) to allow the practitioner to control the reversal of sedation to the approximate endpoint desired and to minimize the possibility of adverse effects (see INDIVIDUALIZATION OF DOSAGE).

Pediatric Patients

For the reversal of the sedative effects of benzodiazepines administered for conscious sedation in pediatric patients greater than 1 year of age, the recommended initial dose is 0.01 mg/kg (up to 0.2 mg) administered intravenously over 15 seconds. If the desired level of consciousness is not obtained after waiting an additional 45 seconds, further injections of 0.01 mg/kg (up to 0.2 mg) can be administered and repeated at 60-second intervals where necessary (up to a maximum of 4 additional times) to a maximum total dose of 0.05 mg/kg or 1 mg, whichever is lower. The dose should be individualized based on the patient’s response. The mean total dose administered in the pediatric clinical trial of flumazenil was 0.65 mg (range: 0.08 mg to 1.00 mg). Approximately one-half of patients required the maximum of five injections.

Resedation occurred in 7 of 60 pediatric patients who were fully alert 10 minutes after the start of flumazenil injection administration (see PRECAUTIONS: Pediatric Use). The safety and efficacy of repeated flumazenil administration in pediatric patients experiencing resedation have not been established.

It is recommended that flumazenil injection be administered as the series of small injections described (not as a single bolus injection) to allow the practitioner to control the reversal of sedation to the approximate endpoint desired and to minimize the possibility of adverse effects (see INDIVIDUALIZATION OF DOSAGE).

The safety and efficacy of flumazenil injection in the reversal of conscious sedation in pediatric patients below the age of 1 year have not been established.

Reversal of General Anesthesia in Adult Patients

For the reversal of the sedative effects of benzodiazepines administered for general anesthesia, the recommended initial dose of flumazenil injection is 0.2 mg (2 mL) administered intravenously over 15 seconds. If the desired level of consciousness is not obtained after waiting an additional 45 seconds, a further dose of 0.2 mg (2 mL) can be injected and repeated at 60-second intervals where necessary (up to a maximum of 4 additional times) to a maximum total dose of 1 mg (10 mL). The dosage should be individualized based on the patient’s response, with most patients responding to doses of 0.6 mg to 1 mg (see INDIVIDUALIZATION OF DOSAGE).

In the event of resedation, repeated doses may be administered at 20-minute intervals as needed. For repeat treatment, no more than 1 mg (given as 0.2 mg/min) should be administered at any one time, and no more than 3 mg should be given in any one hour.

It is recommended that flumazenil injection be administered as the series of small injections described (not as a single bolus injection) to allow the practitioner to control the reversal of sedation to the approximate endpoint desired and to minimize the possibility of adverse effects (see INDIVIDUALIZATION OF DOSAGE).

Management of Suspected Benzodiazepine Overdose in Adult Patients

For initial management of a known or suspected benzodiazepine overdose, the recommended initial dose of flumazenil injection is 0.2 mg (2 mL) administered intravenously over 30 seconds. If the desired level of consciousness is not obtained after waiting 30 seconds, a further dose of 0.3 mg (3 mL) can be administered over another 30 seconds. Further doses of 0.5 mg (5 mL) can be administered over 30 seconds at 1-minute intervals up to a cumulative dose of 3 mg.

Do not rush the administration of flumazenil injection. Patients should have a secure airway and intravenous access before administration of the drug and be awakened gradually (see PRECAUTIONS).

Most patients with a benzodiazepine overdose will respond to a cumulative dose of 1 mg to 3 mg of flumazenil injection, and doses beyond 3 mg do not reliably produce additional effects. On rare occasions, patients with a partial response at 3 mg may require additional titration up to a total dose of 5 mg (administered slowly in the same manner).

If a patient has not responded 5 minutes after receiving a cumulative dose of 5 mg of flumazenil injection, the major cause of sedation is likely not to be due to benzodiazepines, and additional flumazenil injection is likely to have no effect.

In the event of resedation, repeated doses may be given at 20-minute intervals if needed. For repeat treatment, no more than 1 mg (given as 0.5 mg/min) should be given at any one time and no more than 3 mg should be given in any one hour.

Safety and Handling

Flumazenil injection is supplied in sealed dosage forms and poses no known risk to the healthcare provider. Routine care should be taken to avoid aerosol generation when preparing syringes for injection, and spilled medication should be rinsed from the skin with cool water.

HOW SUPPLIED

5 mL multiple dose vial containing 0.1 mg/mL flumazenil (NDC 84549-784-10).

STORAGE

Store at 25ºC (77ºF); excursions permitted to 15º to 30ºC (59º to 86ºF) [See USP Controlled Room Temperature].

Manufactured by:HIKMA FARMACÊUTICA (PORTUGAL), S.A..
Estrada do Rio da Mó, nº 8, 8A e 8B - Fervença - 2705 – 906 Terrugem SNT, PORTUGAL